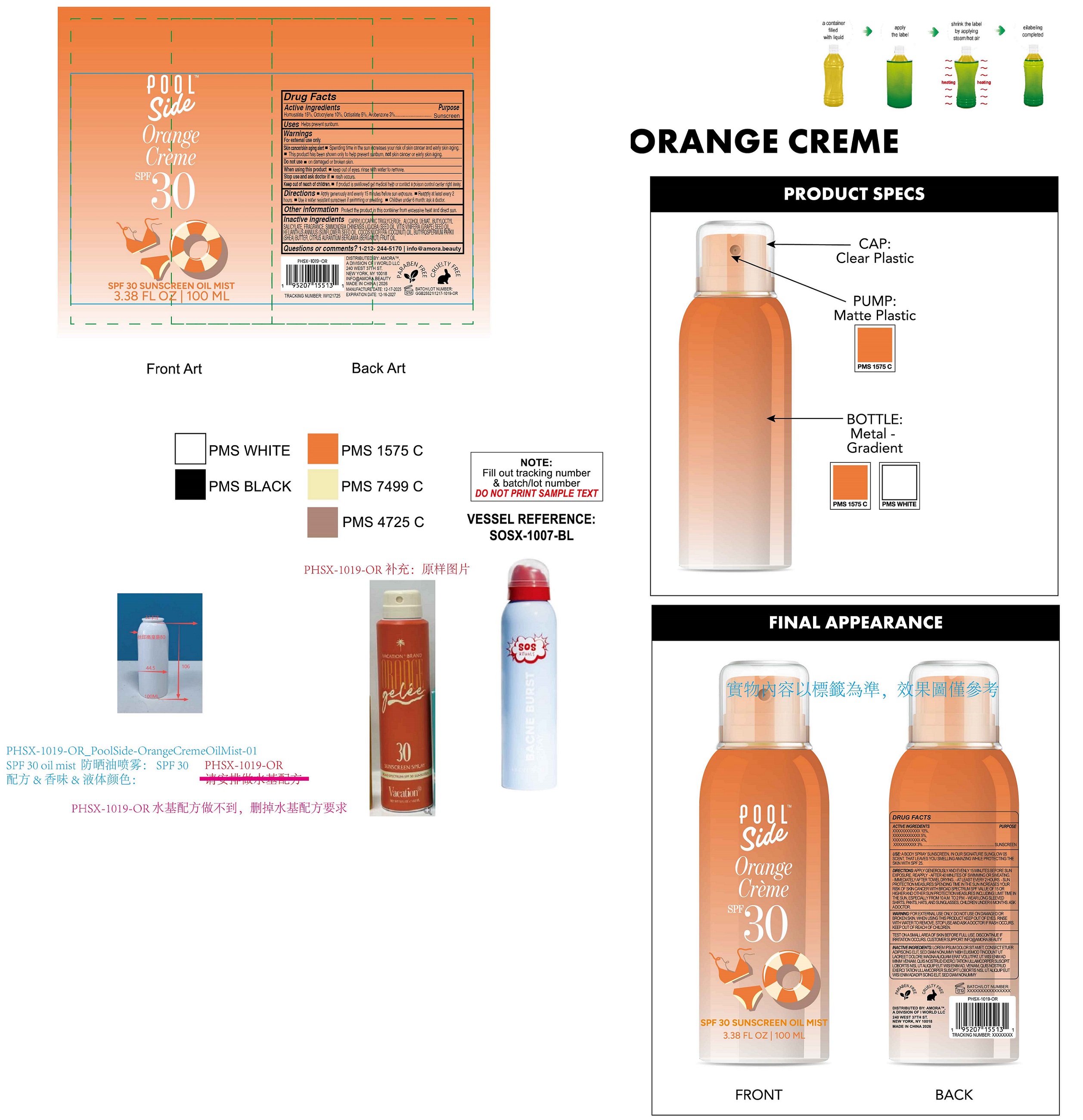 DRUG LABEL: Poolside Orange Creme SPF 30 Sunscreen Oil Mist
NDC: 85179-018 | Form: LIQUID
Manufacturer: I World LLC
Category: otc | Type: HUMAN OTC DRUG LABEL
Date: 20260105

ACTIVE INGREDIENTS: HOMOSALATE 150 mg/1 mL; OCTOCRYLENE 100 mg/1 mL; OCTISALATE 50 mg/1 mL; AVOBENZONE 30 mg/1 mL
INACTIVE INGREDIENTS: MEDIUM-CHAIN TRIGLYCERIDES; ALCOHOL; BUTYLOCTYL SALICYLATE; JOJOBA OIL; GRAPE SEED OIL; SUNFLOWER OIL; COCONUT OIL; SHEA BUTTER; BERGAMOT OIL

Poolside Orange Creme SPF 30 Sunscreen Oil Mist

Active ingredients

Homosalate 15%, Octocrylene 10%, Octisalate 5%, Avobenzone 3%

Purpose

Sunscreen

Uses

Helps prevent sunburn.

Warnings

For external use only.

Skin cancer/skin aging alert

- Spending time in the sun increases your risk of skin cancer and early skin aging.
- This product has been shown only to help prevent sunburn, not skin cancer or early skin aging.

Do not use

- on damaged or broken skin.

When using this product

- keep out of eyes. rinse with water to remove.

Stop use and ask doctor if

- rash occurs.

Keep out of reach of children.

- If product is swallowed get medical help or contact a poison control center right away.

Directions

- Apply generously and evenly 15 minutes before sun exposure.
- Reapply at least every 2 hours
- Use a water resistant sunscreen if swimming or sweating.
- Children under 6 month: ask a doctor.

Other information

Protect the product in this container from excessive heat and direct sun.

Inactive ingredients

CAPRYLIC/CAPRIC TRIGLYCERIDE, ALCOHOL DENAT., BUTYLOCTYL SALICYLATE, FRAGRANCE, SIMMONDSIA CHINENSIS (JOJOBA) SEED OIL, VITIS VINIFERA (GRAPE) SEED OIL, HELIANTHUS ANNUUS (SUNFLOWER) SEED OIL, COCOS NUCIFERA (COCONUT) OIL, BUTYROSPERMUM PARKII (SHEA) BUTTER, CITRUS AURANTIUM BERGAMIA (BERGAMOT) FRUIT OIL.

Questions or comments?

1-212- 244-5170 info@amora.beauty